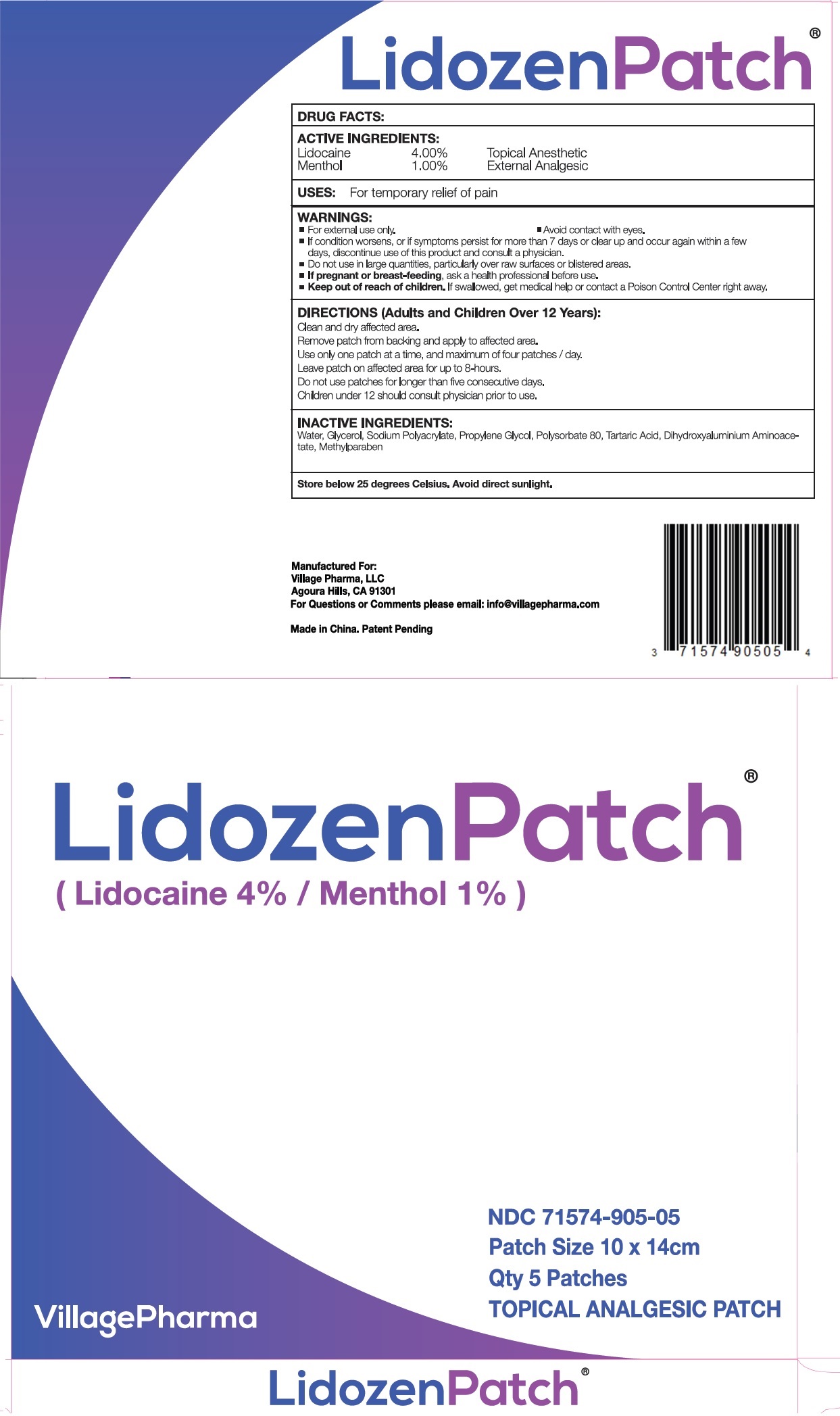 DRUG LABEL: Lidozen Patch
NDC: 71574-905 | Form: PATCH
Manufacturer: Village Pharma LLC
Category: otc | Type: HUMAN OTC DRUG LABEL
Date: 20260101

ACTIVE INGREDIENTS: LIDOCAINE 40 mg/1 g; MENTHOL, UNSPECIFIED FORM 10 mg/1 g
INACTIVE INGREDIENTS: WATER; GLYCERIN; PROPYLENE GLYCOL; POLYSORBATE 80; TARTARIC ACID; DIHYDROXYALUMINUM AMINOACETATE; METHYLPARABEN

Lidozen Patch

ACTIVE INGREDIENTS:

Lidocaine 4.00%

Menthol 1.00%

PURPOSE

Topical Anesthetic

External Analgesic

USES:

For temporary relief of pain

WARNINGS:

- For external use only.
- Avoid contact with eyes.
- If condition worsens, or if symptoms persist for more than 7 days or clear up and occur again within a few days, discontinue use of this product and consult a physician.

Do not use

- in large quantities, particularly over raw surfaces or blistered areas.

If pregnant or breast-feeding,

- ask a health professional before use.

Keep out of reach of children.

- If swallowed, get medical help or contact a Poison Control Center right away.

DIRECTIONS (Adults and Children Over 12 Years):

Clean and dry affected area.

Remove patch from backing and apply to affected area.

Use only one patch at a time, and maximum of four patches / day.

Leave patch on affected area for up to 8-hours.

Do not use patches for longer than five consecutive days.

Children under 12 should consult physician prior to use.

INACTIVE INGREDIENTS

Water, Glycerol, Sodium Polyacrylate, Propylene Glycol, Polysorbate 80, Tartaric Acid, Dihydroxyaluminium Aminoacetate, Methylparaben

Store below 25 degrees Celsius. Avoid direct sunlight.